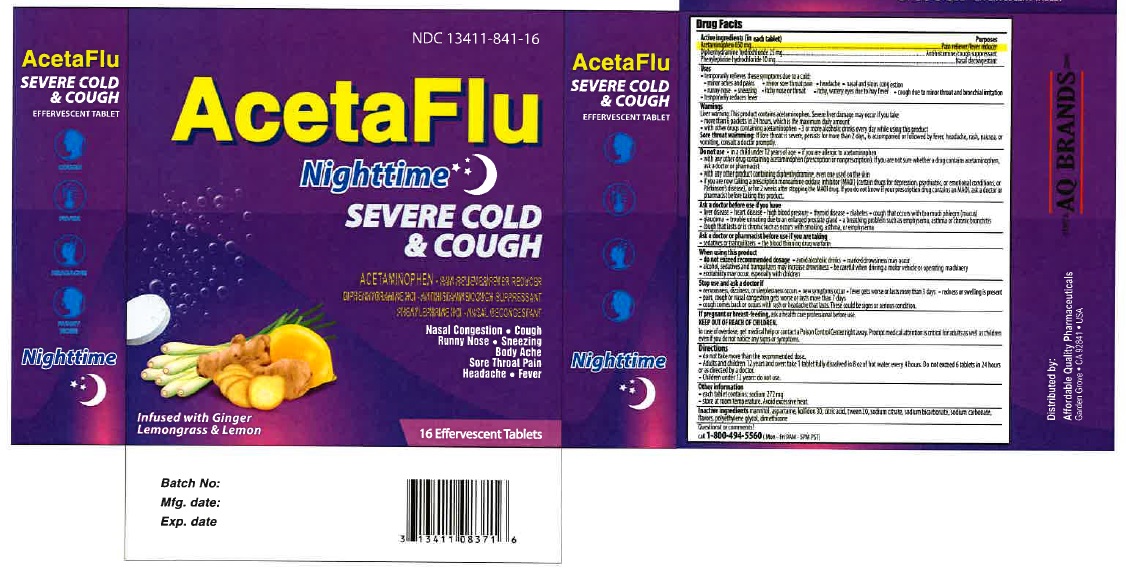 DRUG LABEL: AcetaFlu NightTime Effervescent
NDC: 13411-841 | Form: TABLET, EFFERVESCENT
Manufacturer: Advanced Pharmaceutical Services, Inc. Dba Affordable Quality Pharmaceuticals
Category: otc | Type: HUMAN OTC DRUG LABEL
Date: 20200326

ACTIVE INGREDIENTS: ACETAMINOPHEN 650 mg/1 1; DIPHENHYDRAMINE HYDROCHLORIDE 25 mg/1 1; PHENYLEPHRINE HYDROCHLORIDE 10 mg/1 1
INACTIVE INGREDIENTS: MANNITOL; ASPARTAME; POVIDONE K30; ANHYDROUS CITRIC ACID; POLYSORBATE 20; SODIUM CITRATE; SODIUM BICARBONATE; SODIUM CARBONATE; POLYETHYLENE GLYCOL, UNSPECIFIED; DIMETHICONE

Active ingredients (in each tablet) Purposes

Acetaminophen 650 mg.................................................................................Pain reliever/fever reducer
Diphennhydramine Hydrochloride 25 mg.........................................................Antihistamine/ Cough suppressant
Phenylephrine Hydrochloride 10 mg................................................................Nasal decongestant

Uses
• temporarily relieves these symptoms due to a cold:
• minor aches and pains • minor sore throat pain • headache
• nasal and sinus congestion • cough due to minor throat and bronchial irritation
• temporarily reduces fever

Warnings
Liver warning: This product contains acetaminophen. Severe liver damage may occur if you take
• more than 6 tablets in 24 hours, which is the maximum daily amount
• with other drugs containing acetaminophen • 3 or more alcoholic drinks every day while using this product
Sore throat warning: If sore throat is severe, persists for more than 2 days, is accompanied or followed by fever, headache, rash, nausea, or vomiting, consult a doctor promptly.

Do not use • in a child under 12 years of age • if you are allergic to acetaminophen
• with any other drug containing acetaminophen (prescription or nonprescription). If you are not sure whether a drug contains acetaminophen,

ask a doctor or pharmacist
• if you are now taking a prescription monoamine oxidase inhibitor (MAOI) (certain drugs for depression, psychiatric, or emotional conditions, or Parkinson’s disease), or for 2 weeks after stopping the MAOI drug. If you do not know if your prescription drug contains an MAOI, ask a doctor or pharmacist before taking this product.

Ask a doctor before use if you have
• liver disease • heart disease • high blood pressure • thyroid disease • diabetes
• trouble urinating due to an enlarged prostate gland • cough that occurs with too much phlegm (mucus)
• cough that lasts or is chronic such as occurs with smoking, asthma, or emphysema

Ask a doctor or pharmacist before use if you are • taking the blood thinning drug warfarin

When using this product • do not exceed recommended dosage. avoid alcoholic drinks marked drowsiness may occur.

Alcohol, sedatives and tranquilizes may increase drowsiness be careful when driving a motor vehicle or operating machinery

excitability may occur, especially with children.

Stop use and ask a doctor if
• nervousness, dizziness, or sleeplessness occurs • fever gets worse or lasts more than 3 days
• redness or swelling is present • new symptoms occur • symptoms do not get better or worsen
• pain, cough or nasal congestion gets worse or lasts more than 7 days
• cough comes back or occurs with fever, rash or headache that lasts. These could be signs or serious condition.

If pregnant or breast-feeding, ask a health care professional before use.

KEEP OUT OF REACH OF CHILDREN.
In case of overdose, get medical help or contact a Poison Control Center right away. Prompt medical attention is
critical for adults as well as children even if you do not notice any signs or symptoms.

Directions
• do not take more than the the recommended dose
• adults and children 12 years and over: take 1 tablet fully dissolved in 8 oz of water every 4 hours. Do not exceed 6 tablets in 24 hours or as directed by a doctor
• children under 12 years: do not use

Other information
• each tablet contains: sodium 272 mg
• store at room temperature. Avoid excessive heat .

Inactive ingredients

mannitol, aspartame, kollidon 30, citric acid, tween 20, sodium citrate, sodium bicarbonate, sodium carbonate, flavors, polyethylene glycol,

dimethicone